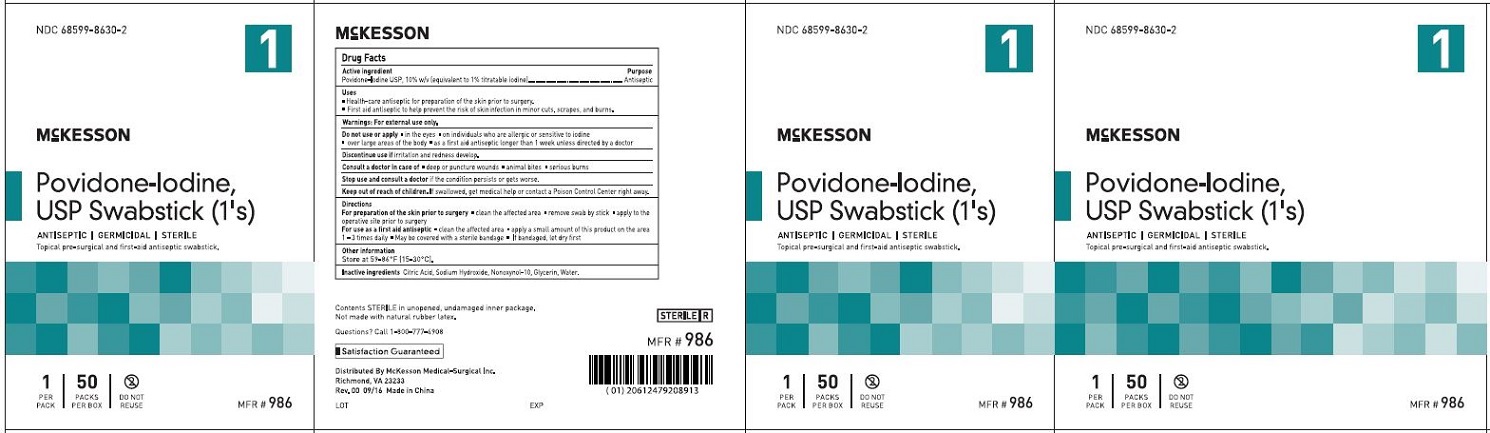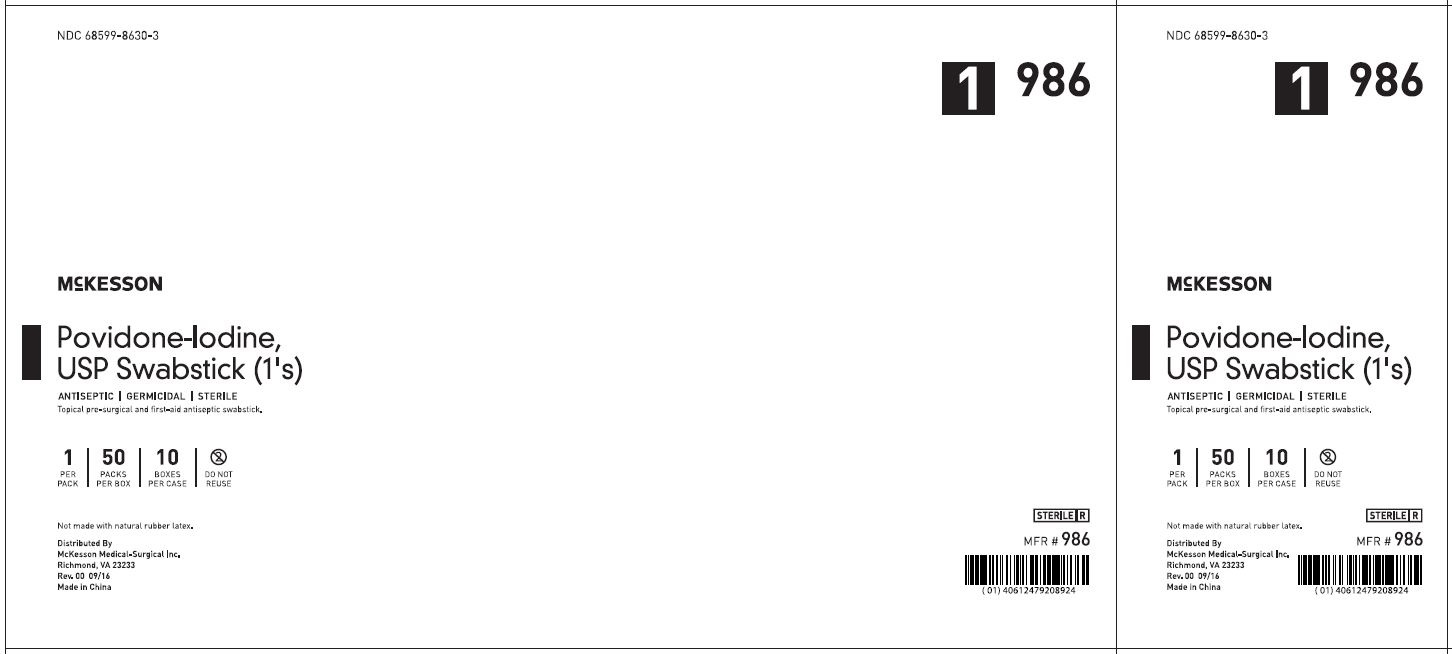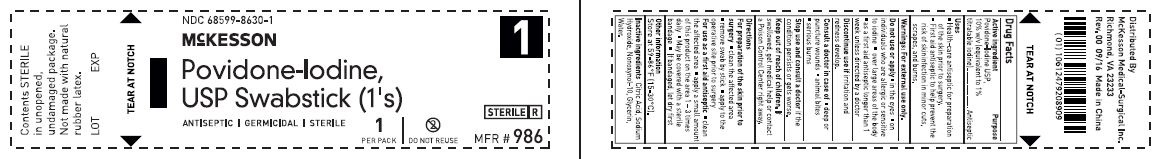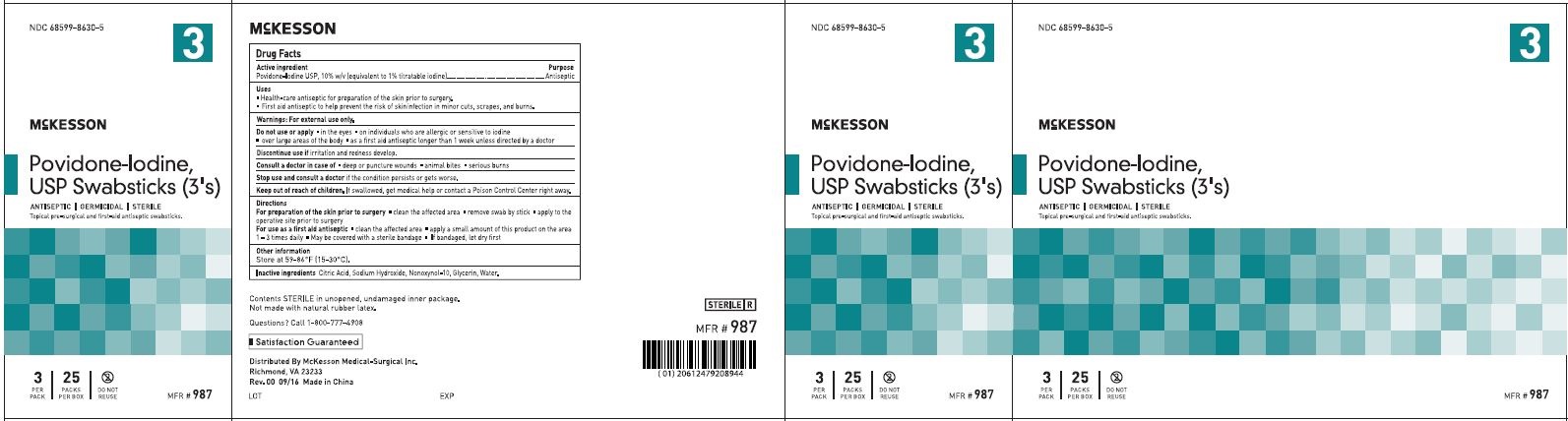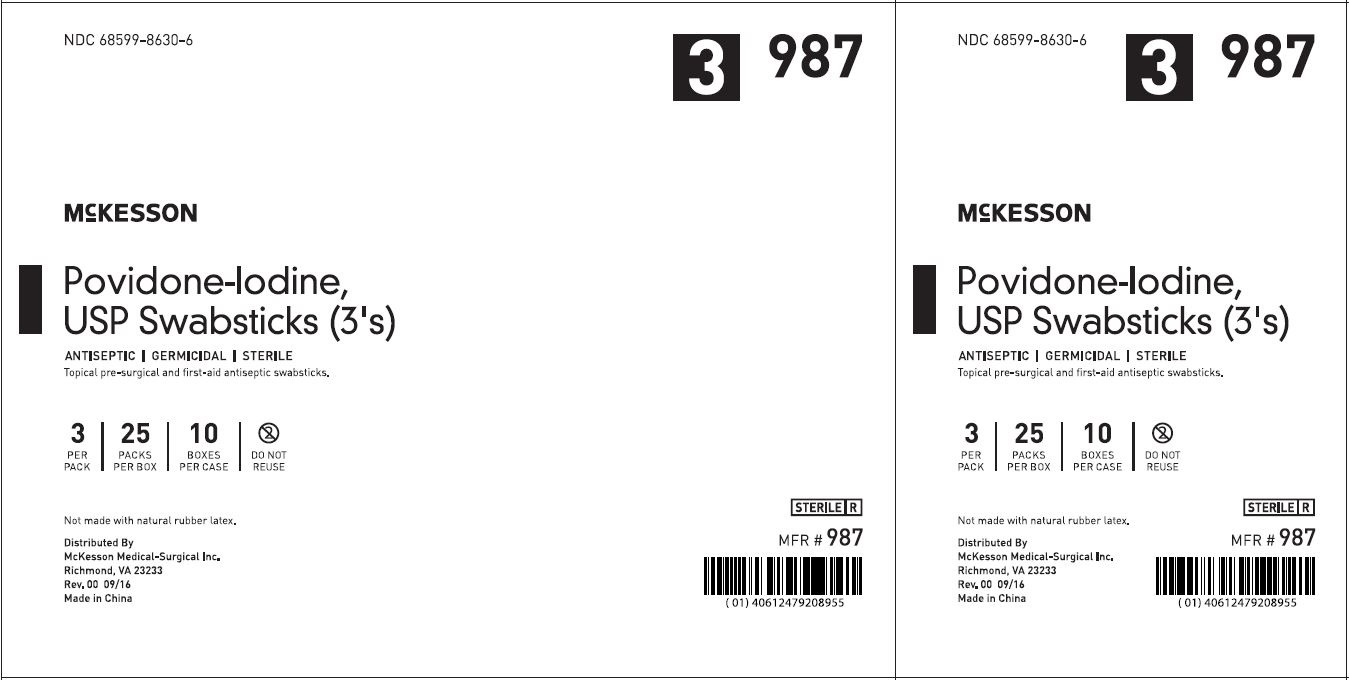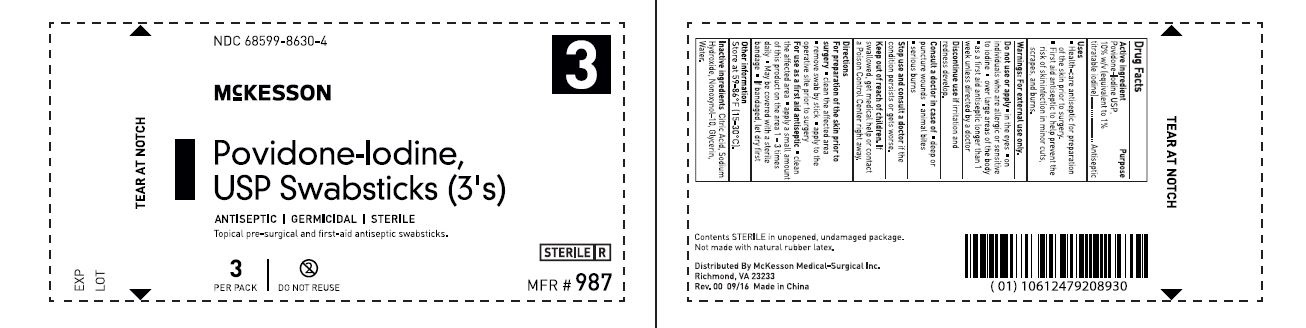 DRUG LABEL: Swab
NDC: 68599-8630 | Form: SWAB
Manufacturer: McKesson Medical-Surgical Inc.
Category: otc | Type: HUMAN OTC DRUG LABEL
Date: 20241014

ACTIVE INGREDIENTS: POVIDONE-IODINE 10 mg/1 1
INACTIVE INGREDIENTS: CITRIC ACID MONOHYDRATE; SODIUM HYDROXIDE; NONOXYNOL-10; GLYCERIN; WATER

ACTIVE INGREDIENT

Povidone-Iodine USP, 10% w/v (equivalent to 1% titratable iodine)

PURPOSE

Antiseptic

INDICATIONS AND USAGE

Health-care antiseptic for preparation of the skin prior to surgery.

First aid antiseptic to help prevent the risk of skin infection in minor cuts, scrapes, and burns.

WARNINGS

For external use only.

Do not use or apply• in the eyes • on individuals who are allergic or sensitive to iodine • over large areas of the body • as a first aid antiseptic longer than 1 week unless directed by a doctor

Discontinue use ifirritation and redness develop

Consult a doctor in case of• deep or puncture wounds • animal bites • serious burns

Stop use and consult a doctorif the condition persists or gets worse

Keep out of reach of children.If swallowed, get medical help or contact a Poison Control Center right away.

DOSAGE AND ADMINISTRATION

For preparation of the skin prior to surgery• clean the affected area • remove swab by stick • apply to the operative site prior to surgery

For use as a first aid antiseptic• clean the affected area • apply a small amount of this product on the area 1 - 3 times daily • May be covered with a sterile bandage • If bandaged, let dry first

OTHER SAFETY INFORMATION

Store at 59-86ºF (15-30ºC).

INACTIVE INGREDIENT

Citric Acid, Sodium Hydroxide, Nonoxynol-10, Glycerin, Water.